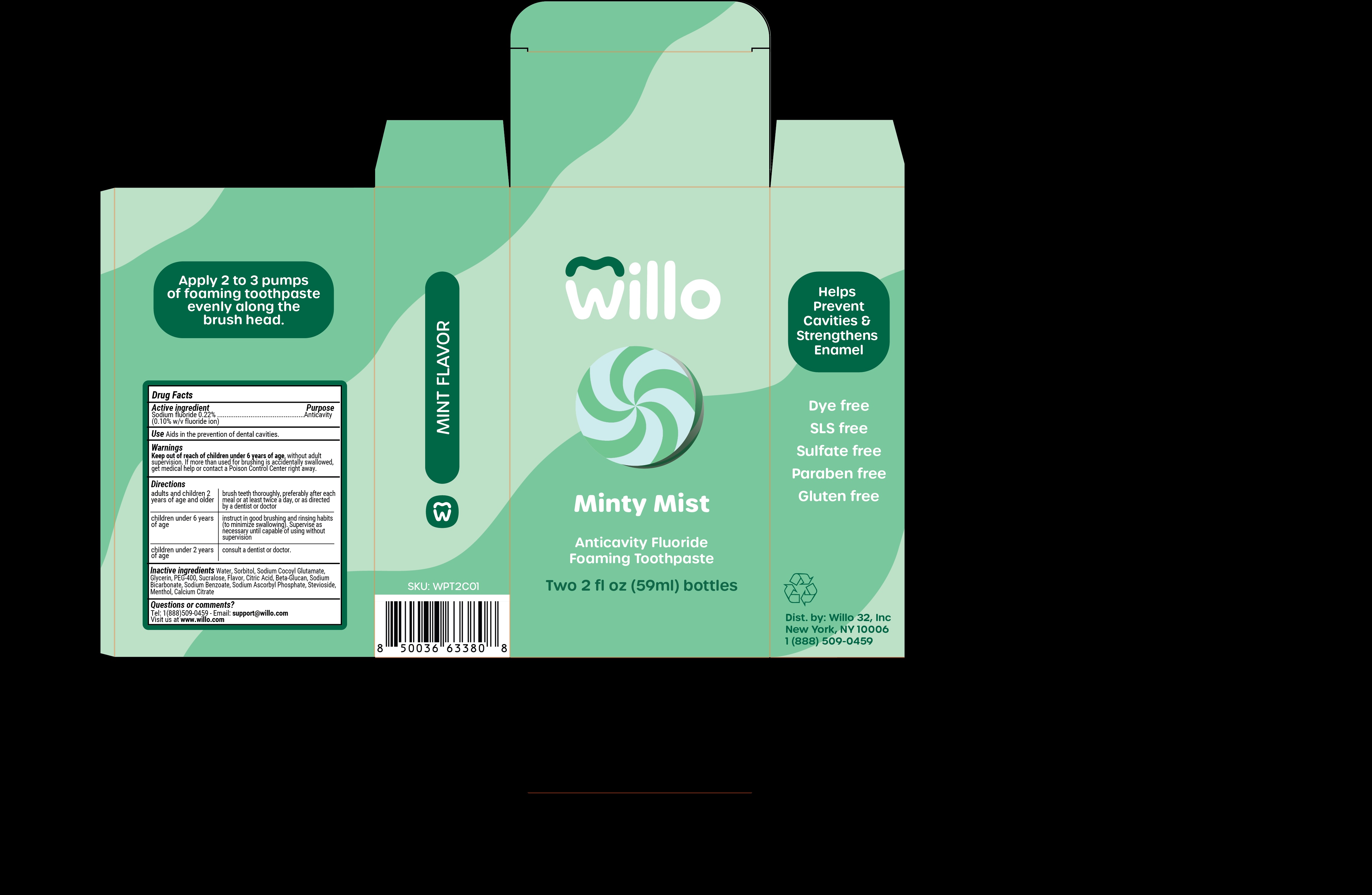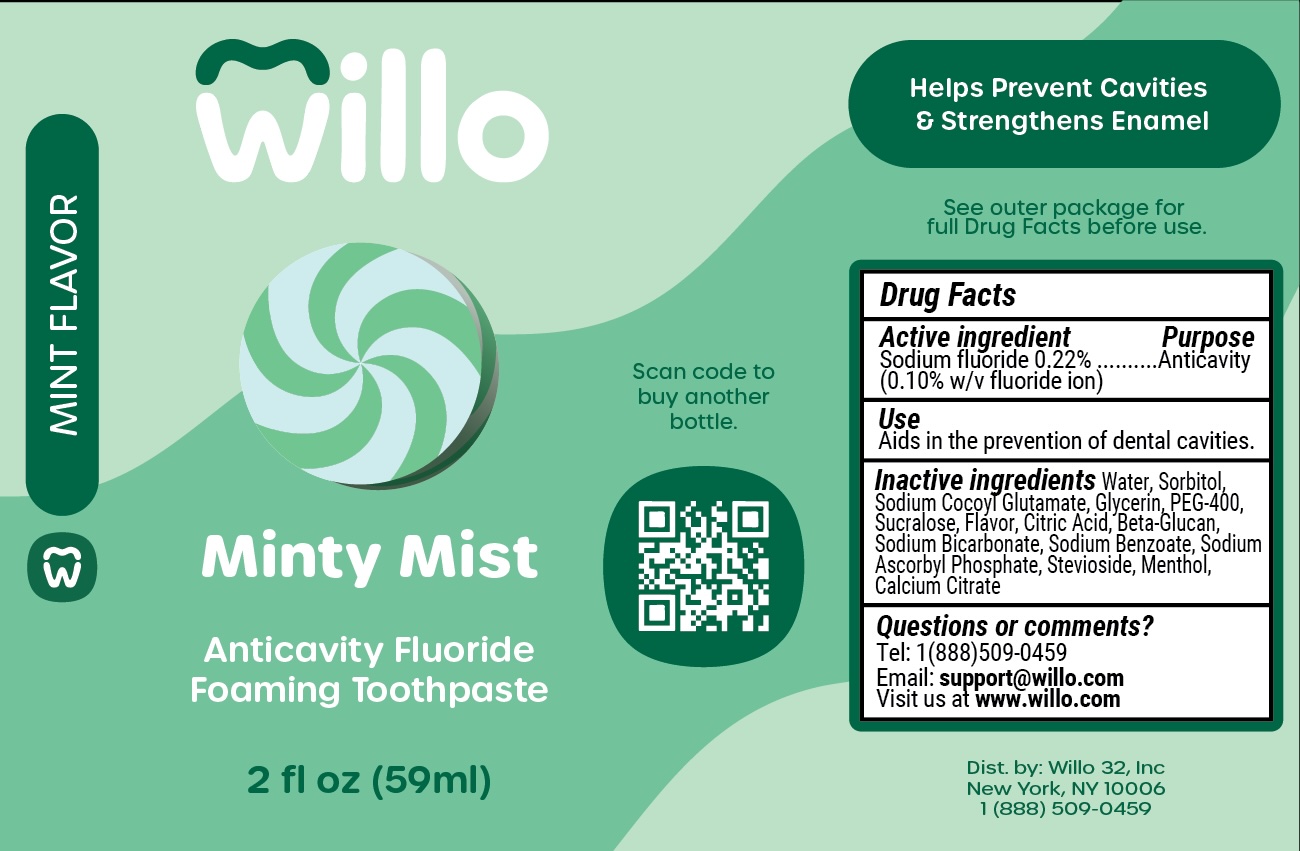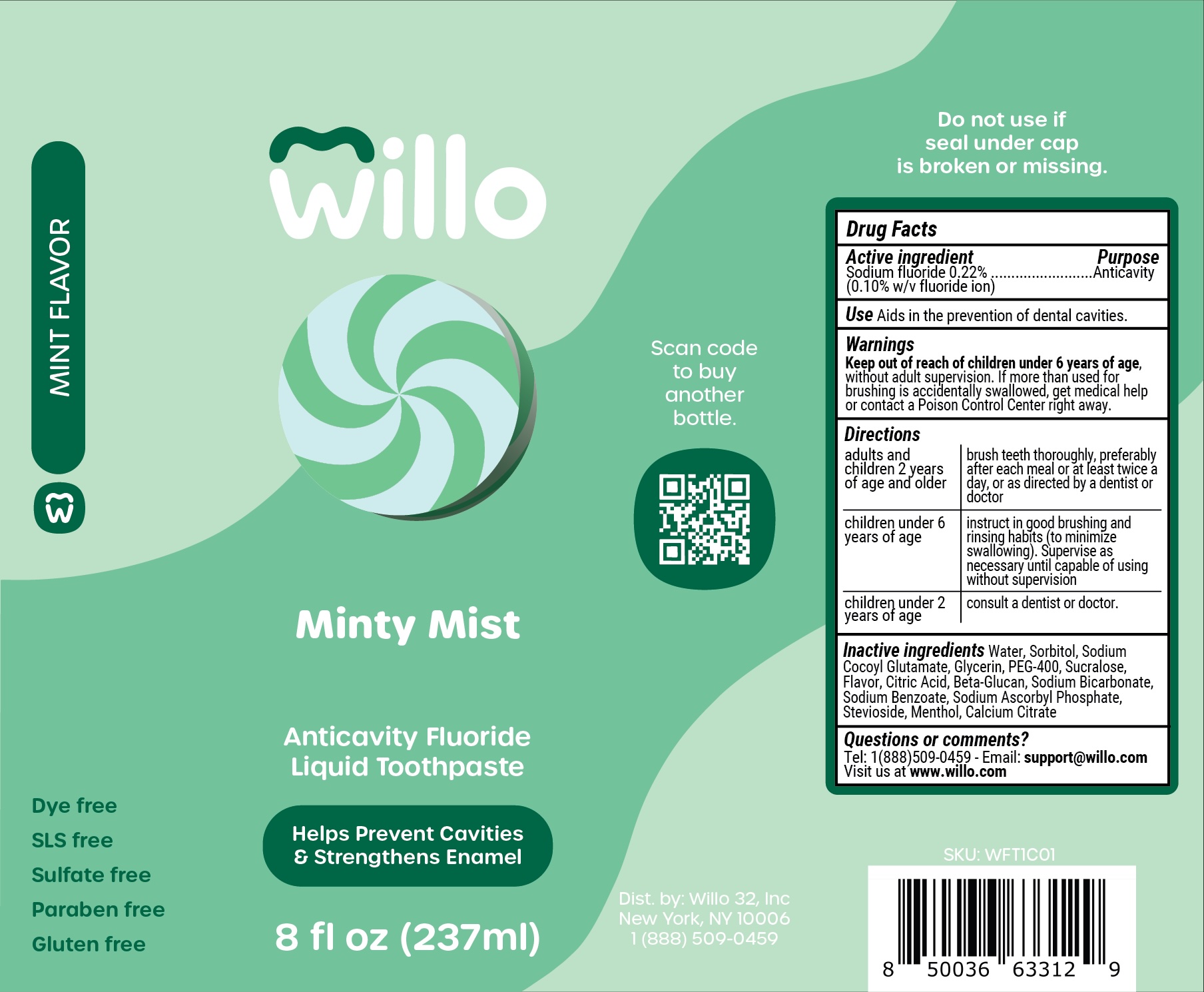 DRUG LABEL: Willo Minty Mist Dye Free
NDC: 84185-302 | Form: PASTE, DENTIFRICE
Manufacturer: Willo 32, Inc.
Category: otc | Type: HUMAN OTC DRUG LABEL
Date: 20250916

ACTIVE INGREDIENTS: SODIUM FLUORIDE 1 mg/1 mL
INACTIVE INGREDIENTS: SORBITOL; SODIUM BENZOATE; CALCIUM CITRATE; SODIUM BICARBONATE; YEAST .BETA.-D-GLUCAN; PEG-400; SODIUM COCOYL GLUTAMATE; STEVIOSIDE; MENTHOL; SODIUM ASCORBYL PHOSPHATE; WATER; GLYCERIN; SUCRALOSE; CITRIC ACID

Drug Facts

Active ingredient

Sodium fluoride 0.22%

(0.10% w/v fluoride ion)

Purpose

Anticavity

Use

Use Aids in the prevention of dental cavities

Warnings

Keep out of reach of children under 6 years of age, without adult supervision. If more than used for brushing is accidentally swallowed, get medical help or contact a Poison Control Center right away.

Directions

adults and children 2 years of age and older | brush teeth thoroughly, preferably after each meal or at least twice a day, or as directed by a dentist or doctor
children under 6 years of age | instruct in good brushing habits (to minimize swallowing). Supervise as necessary until capable or using without supervision
children under 2 years of age | consult with a dentist or doctor

Inactive ingredients

Inactive ingredients Water, Sorbitol, Sodium Cocoyl Glutamate, Glycerin, PEG-400, Sucralose, Flavor, Citric Acid, Beta-Glucan, Sodium Bicarbonate, Sodium Benzoate, Sodium Ascorbyl Phosphate, Stevioside, Menthol, Calcium Citrate

Questions or comments

Tel: 1(888)509-0459 - Email: support@willo.com

Visit us at www.willo.com

Broken seal warning

Do not use if seal under cap is broken or missing

Flavor description

MINT FLAVOR

Free of claims

Dye free

SLS free

Sulfate free

Paraben free

Gluten free

PACKAGE LABEL

Willo

Minty Mist

Anticavity Fluoride

Liquid Toothpaste

Helps Prevent Cavities

& Strengthens Enamel

8 fl oz (237 ml)

Scan code to buy another bottle

Dist. by: Willo 32, Ince

New York, NY 10006

1 (888) 509-0459